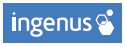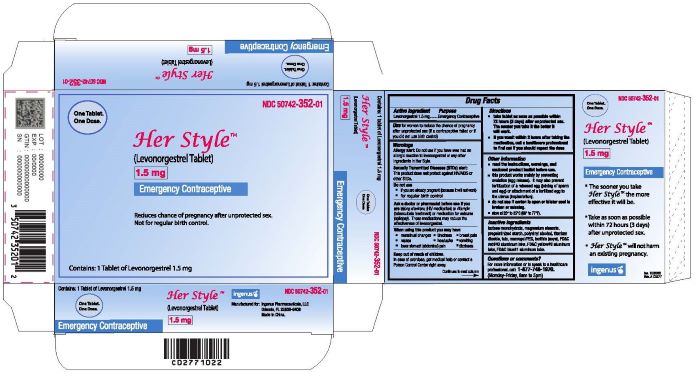 DRUG LABEL: Her Style
NDC: 50742-352 | Form: TABLET
Manufacturer: Ingenus Pharmaceuticals, LLC
Category: otc | Type: HUMAN OTC DRUG LABEL
Date: 20251205

ACTIVE INGREDIENTS: LEVONORGESTREL 1.5 mg/1 1
INACTIVE INGREDIENTS: MAGNESIUM STEARATE; LACTOSE MONOHYDRATE; STARCH, PREGELATINIZED CORN; POLYVINYL ALCOHOL; TITANIUM DIOXIDE; TALC; POLYETHYLENE GLYCOL 3350; LECITHIN, SOYBEAN; FD&C RED NO. 40; FD&C YELLOW NO. 6; FD&C BLUE NO. 1

Her Style™ (Levonorgestrel Tablet, 1.5mg)

ACTIVE INGREDIENT

Levonorgestrel 1.5mg

PURPOSE

Emergency contraception

USE

Use for women to reduce the chance of pregnancy after unprotected sex (if a contraceptive failed or if you did not use birth control)

WARNINGS

Allergy alert: Do not use if you have ever had an allergic reaction to levonorgestrel or any other ingredients in Her Style.

Sexually transmitted diseases (STDs) alert: This product does not protect against HIV/AIDS or other STDs

Do not use

•if you are already pregnant (because it will not work)

•for regular birth control

Ask a doctor or pharmacist before use if you are taking efavirenz (HIV medication) or rifampin (tuberculosis treatment) or medication for seizures (epilepsy). These medications may reduce the effectiveness of levonorgestrel.

When using this product you may have

• menstrual changes

• nausea

• lower stomach (abdominal) pain

• tiredness

• headache

• dizziness

• breast pain

• vomiting

KEEP OUT OF REACH OF CHILDREN

In case of overdose, get medical help or contact a Poison Control center right away.

DIRECTIONS

•take as soon as possible within 72 hours (3 days) after unprotected sex. The sooner you take it the better it will work.

•if you vomit within 2 hours after taking the medication, call a healthcare professional to find out if you should repeat the dose

OTHER INFORMATION

•read the instructions, warnings and enclosed product leaflet before use.

•this product works mainly by preventing ovulation (egg release). It may also prevent fertilization of a released egg (joining of sperm and egg) or attachment of a fertilized egg to the uterus (implantation).

•do not use if carton is open or blister seal is broken or missing.

•Store at 20° to 25°C (68° to 77°F).

INACTIVE INGREDIENT

magnesium stearate, lactose monohydrate, pregelatinized starch, polyvinyl alcohol, titanium dioxide, talc, macrogol/PEG, lecithin (soya), FD&C red#40 aluminum lake, FD&C yellow#6 aluminum lake, FD&C blue#1 aluminum lake.

QUESTIONS OR COMMENTS?

For more information or to speak to a healthcare professional, call: 1-877-748-1970.

(Monday-Friday, 9am to 5pm)

Her Style™

(levonorgestrel Tablet) 1.5 mg

Emergency Contraceptive

One Tablet. One Dose.

What You Need to Know What is Her Style™?

Her Style™ is emergency contraception that helps prevent pregnancy after birth control failure or unprotected sex. It is a backup method of preventing pregnancy and should not be used as regular birth control.

What Her Style™ is not.

Her Style™ will not work if you are already pregnant and will not affect an existing pregnancy. Her Style™ will not protect you from HIV infection (the virus that causes AIDS) and other sexually transmitted diseases (STDs).

When should I use Her Style™?

The sooner you take emergency contraception, the better it works. You should use Her Style™ within 72 hour s (3 days) after you have had unprotected sex.

Her Style™ is a backup or emergency method of birth control you can use when:

•your regular birth control was used incorrectly or failed

•you did not use any birth control method

When not to use Her Style™.

Her Style™ should not be used:

•as a regular birth control method, because it's not as effective as regular birth control.

•if you are already pregnant, because it will not work.

•if you are allergic to levonorgestrel or any other ingredients in Her Style™.

When should I talk to a doctor or pharmacist?

Ask a doctor or pharmacist before use if you are taking efavirenz (HIV medication) or rifampin (tuberculosis treatment) or medication for seizures (epilepsy). These medications may reduce the effectiveness of Her Style™ and increase your chance of becoming pregnant. Your doctor may prescribe another form of emergency contraception that may not be affected by these medications.

How does Her Style™ work?

Her Style™ is one tablet with levonorgestrel, a hormone that has been used in many birth control pills for several decades. Her Style™ contains a higher dose of levonorgestrel than birth control pills, but works in a similar way to prevent pregnancy. It works mainly by stopping the release of an egg from the ovary. It is possible that Her Style™ may also work by preventing fertilization of an egg (the uniting of sperm with the egg) or by preventing attachment (implantation) to the uterus (womb).

How can I get the best results from Her Style™?

You have 72 hours (3 days) to try to prevent pregnancy after birth control failure or unprotected sex. The sooner you take Her Style™, the better it works.

How effective is Her Style™?

If Her Style™ is taken as directed, it can significantly decrease the chance that you will get pregnant. About 7 out of every 8 women who would have gotten pregnant will not become pregnant.

How will I know Her Style™ worked?

You will know Her Style™ has been effective when you get your next period, which should come at the expected time, or within a week of the expected time. If your period is delayed beyond 1 week, it is possible you may be pregnant. You should get a pregnancy test and follow up with your healthcare professional.

Will I experience any side effects?

•some women may have changes in their period, such as a period that is heavier or lighter or a period that is early or late. If your period is more than a week late, you may be pregnant.

•if you have severe abdominal pain, you may have an ectopic pregnancy, and should get immediate medical attention.

•when used as directed, Her Style™ is safe and effective.

Side effects may include changes in your period, nausea, lower stomach (abdominal) pain, tiredness, headache, dizziness, and breast tenderness.

•if you vomit within 2 hours of taking the medication, call a healthcare professional to find out if you should repeat the dose.

What if I still have questions about Her Style™?

If you have questions or need more information, call our toll-free number, 1-877-748-1970.

Other Information

Keep out of reach of children:

In case of overdose, get medical help or contact a Poison Control Center right away at 1-800-222-1222.

Do not use if the blister seal is opened.

Store at room temperature 20° to 25°C (68° to 77°F).

Active ingredient: levonorgestrel 1.5 mg

Inactive ingredients: magnesium stearate, lactose monohydrate, pregelatinized starch, polyvinyl alcohol, titanium dioxide, talc, macrogol/PEG, lecithin (soya), FD&C red#40 aluminum lake, FD&C yellow#6 aluminum lake, FD&C blue#1 aluminum lake.

If you are sexually active, you should see a healthcare provider for routine checkups. Your healthcare provider will talk to you about, and if necessary, test you for sexually transmitted diseases, teach you about effective methods of routine birth control, and answer any other questions you may have.

Manufactured for: Ingenus Pharmaceuticals LLC

Orlando, FL 32839-6408

Made in China.

I0173

Rev. A

Iss. 10/2022